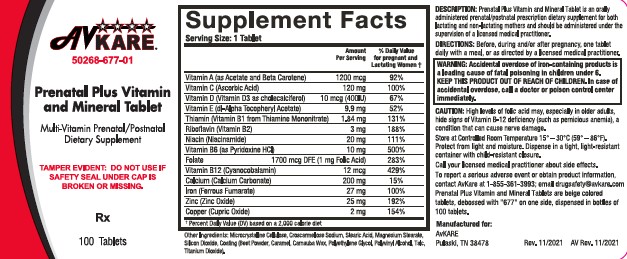 DRUG LABEL: PRENATAL PLUS
NDC: 50268-677 | Form: TABLET, FILM COATED
Manufacturer: AvPAK
Category: prescription | Type: HUMAN PRESCRIPTION DRUG LABEL
Date: 20220412

ACTIVE INGREDIENTS: .ALPHA.-TOCOPHEROL ACETATE, DL- 9.9 mg/1 1; VITAMIN A ACETATE 3080 [iU]/1 1; BETA CAROTENE 920 [iU]/1 1; ASCORBIC ACID 120 mg/1 1; CHOLECALCIFEROL 400 [iU]/1 1; THIAMINE MONONITRATE 1.84 mg/1 1; RIBOFLAVIN 3 mg/1 1; NIACINAMIDE 20 mg/1 1; PYRIDOXINE HYDROCHLORIDE 10 mg/1 1; FOLIC ACID 1 mg/1 1; CYANOCOBALAMIN 12 ug/1 1; CALCIUM CARBONATE 200 mg/1 1; FERROUS FUMARATE 27 mg/1 1; ZINC OXIDE 25 mg/1 1; CUPRIC OXIDE 2 mg/1 1
INACTIVE INGREDIENTS: ASCORBYL PALMITATE; BUTYLATED HYDROXYTOLUENE; CROSCARMELLOSE SODIUM; CALCIUM PHOSPHATE, DIBASIC, DIHYDRATE; .ALPHA.-TOCOPHEROL, DL-; FD&C RED NO. 40; FD&C YELLOW NO. 5; FD&C YELLOW NO. 6; GELATIN; HYPROMELLOSES; MAGNESIUM STEARATE; MALTODEXTRIN; CELLULOSE, MICROCRYSTALLINE; POLYETHYLENE GLYCOL, UNSPECIFIED; PROPYLENE GLYCOL; SILICON DIOXIDE; SODIUM ASCORBATE; SODIUM BENZOATE; SORBIC ACID; STARCH, CORN; STEARIC ACID; SUCROSE; SUNFLOWER OIL; TITANIUM DIOXIDE; TRIACETIN

Prenatal Plus Vitamin and Mineral Tablet
Multi-Vitamin Prenatal / Postnatal
Dietary Supplement
Rx Only

DESCRIPTION

Prenatal Plus Vitamin and Mineral Tablet is an orally administered prenatal / postnatal prescription dietary supplement for both lactating and non-lactating mothers and should be administered under the supervision of a licensed medical practitioner.

INDICATIONS AND USAGE

To provide Vitamin and Mineral supplementation throughout pregnancy and during the postnatal period for both the lactating and non-lactating mother. It is also useful for improving nutritional status prior to conception.

WARNINGS

WARNING: Accidental overdose of iron-containing products is a leading cause of fatal poisoning in children under age 6. Keep this product out of the reach of children. In case of accidental overdose, call a doctor or Poison Control Center immediately.

PRECAUTIONS

High levels of folic acid may, especially in older adults, hide signs of Vitamin B-12 deficiency (such as pernicious anemia), a condition that can cause nerve damage.

Call your licensed medical practitioner about side effects.

To report a serious adverse event or obtain product information, contact AvKARE at 1-855-361-3993; email drugsafety@avkare.com

DOSAGE AND ADMINISTRATION

Before, during and/or after pregnancy, one tablet daily with a meal, or as directed by a licensed medical practitioner.

HOW SUPPLIED

Prenatal Plus Vitamin and Mineral Tablets are beige colored tablets, debossed with "677" on one side, dispensed in bottles of 100 tablets (NDC 50268-677-01)

Storage

STORE AT CONTROLLED ROOM TEMPERATURE 15º to 30ºC (59º to 86ºF).

Protect from light and moisture. Dispense in a tight, light-resistant container with child-resistant closure.

Manufactured for:

AvKARE

Pulaski, TN 38478

Rev. 11/2021

AV Rev. 11/2021